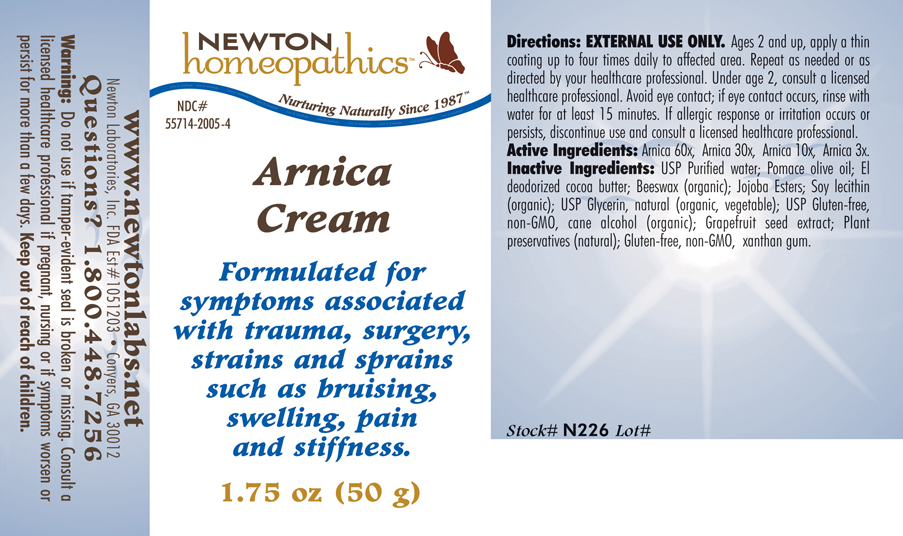 DRUG LABEL: Arnica Cream 
NDC: 55714-2005 | Form: CREAM
Manufacturer: Newton Laboratories, Inc.
Category: homeopathic | Type: HUMAN OTC DRUG LABEL
Date: 20130801

ACTIVE INGREDIENTS: Arnica Montana 60 [hp_X]/1 g
INACTIVE INGREDIENTS: Water; Olive Oil; Cocoa Butter; Royal Jelly; Jojoba Oil; Lecithin, Soybean; Glycerin; Alcohol; Citrus Paradisi Seed; Lonicera Japonica Flower; Xanthan Gum

Arnica Cream

INDICATIONS & USAGE SECTION

Arnica Cream: Formulated for symptoms associated with trauma, surgery, strains and sprains such as bruising, swelling, pain and stiffness.

DOSAGE & ADMINISTRATION SECTION

Directions: EXTERNAL USE ONLY. Ages 2 and up, apply a thin coating up to four times daily to affected area. Repeat as needed or as directed by your healthcare professional. Under age 2, consult a licensed healthcare professional. Avoid eye contact; if eye contact occurs, rinse with water for at least 15 minutes. If allergic response or irritation occurs or persists, discontinue use and consult a licensed healthcare professional.

OTC - ACTIVE INGREDIENT SECTION

Arnica 60x, Arnica 30x, Arnica 10x, Arnica 3x

OTC - PURPOSE SECTION

Formulated for symptoms associated with trauma, surgery, strains and sprains such as bruising, swelling, pain and stiffness.

INACTIVE INGREDIENT SECTION

Inactive Ingredients: USP Purified Water, Pomace Olive Oil, El Deodorized Cocoa Butter, Beeswax (organic), Jojoba Esters, Soy Lecithin (organic), USP Glycerin, natural (organic, vegetable), USP Gluten-free, non-GMO Cane Alcohol (organic), Grapefruit Seed Extract, Plant preservatives (natural), Gluten-free, non-GMO Xanthan Gum.

QUESTIONS SECTION

www.newtonlabs.net Newton Laboratories, Inc. FDA Est # 1051203 - Conyers, GA 30012 Questions? 1.800.448.7256

WARNINGS SECTION

Warning: Do not use if tamper - evident seal is broken or missing. Consult a licensed healthcare professional if pregnant, nursing or if symptoms worsen or persist for more than a few days. Keep out of reach of children.

OTC - PREGNANCY OR BREAST FEEDING SECTION

Consult a licensed healthcare professional if pregnant, nursing or if symptoms worsen or persist for more than a few days.

OTC - KEEP OUT OF REACH OF CHILDREN SECTION

Keep out of reach of children.